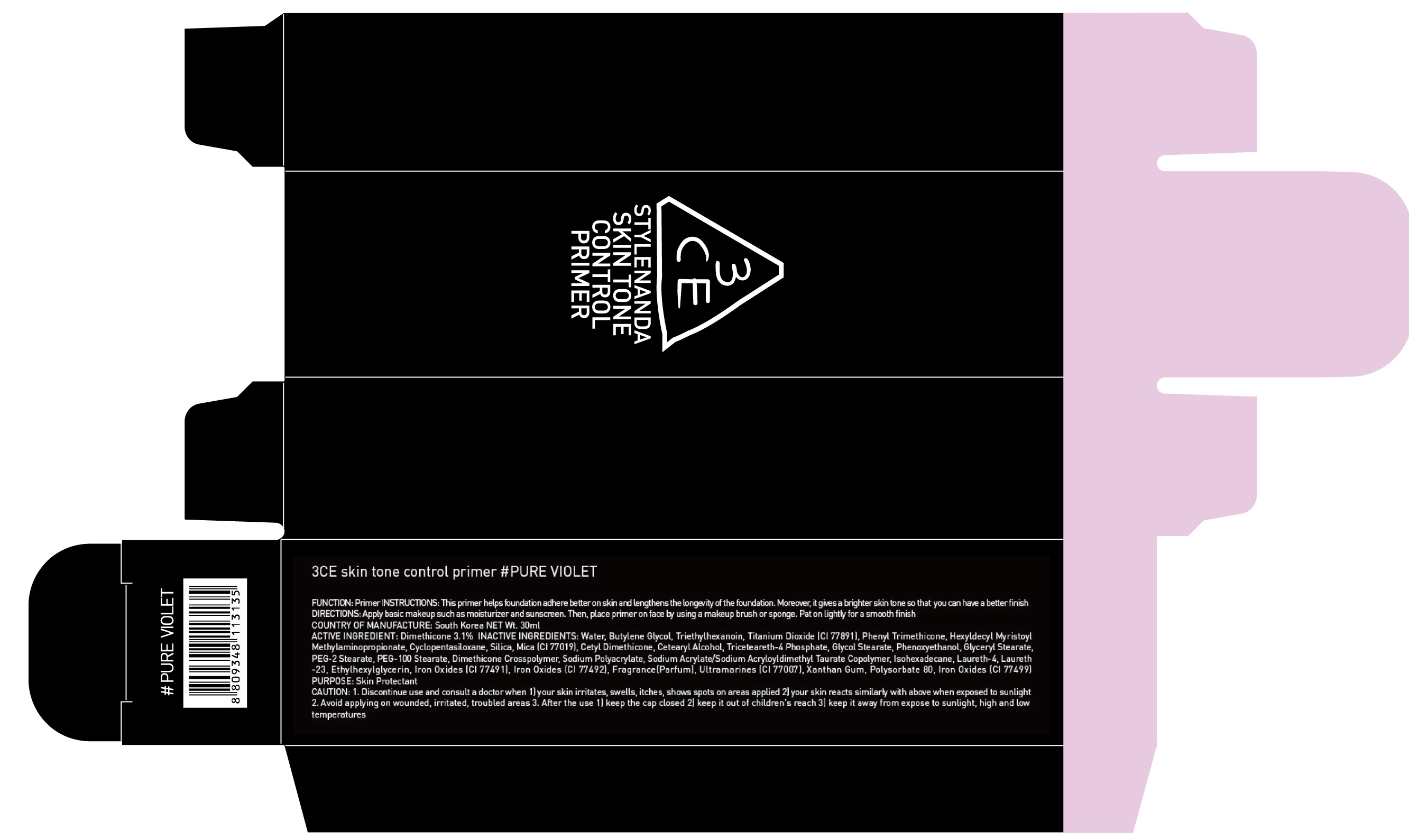 DRUG LABEL: 3CE SKIN TONE CONTROL PRIMER PURE VIOLET
NDC: 60764-128 | Form: CREAM
Manufacturer: Nanda Co., Ltd
Category: otc | Type: HUMAN OTC DRUG LABEL
Date: 20161014

ACTIVE INGREDIENTS: Dimethicone 0.93 g/30 mL
INACTIVE INGREDIENTS: Water; Butylene Glycol

ACTIVE INGREDIENT

Active Ingredient: Dimethicone 3.1%

INACTIVE INGREDIENT

Inactive Ingredients: Water, Butylene Glycol, Triethylhexanoin, Titanium Dioxide (CI 77891), Phenyl Trimethicone, Hexyldecyl Myristoyl Methylaminopropionate, Cyclopentasiloxane, Silica, Mica (CI 77019), Cetyl Dimethicone, Cetearyl Alcohol, Triceteareth-4 Phosphate, Glycol Stearate, Phenoxyethanol, Glyceryl Stearate, PEG-2 Stearate, PEG-100 Stearate, Dimethicone Crosspolymer, Sodium Polyacrylate, Sodium Acrylate/Sodium Acryloyldimethyl Taurate Copolymer, Isohexadecane, Laureth-4, Laureth-23, Ethylhexylglycerin, Iron Oxides (CI 77491), Iron Oxides (CI 77492), Fragrance(Parfum), Ultramarines (CI 77007), Xanthan Gum, Polysorbate 80, Iron Oxides (CI 77499)

PURPOSE

Purpose: Skin Protectant

CAUTION

CAUTION: 1. Discontinue use and consult a doctor when - your skin irritates, swells, itches, shows spots on areas applied - your skin reacts similarly with above when exposed to sunlight 2. Avoid applying on wounded, irritated, troubled areas 3. After the use - keep the cap closed - keep it out of children's reach - keep it away from expose to sunlight, high and low temperatures

KEEP OUT OF REACH OF CHILDREN

keep it out of children's reach

INSTRUCTIONS

INSTRUCTIONS: This primer helps foundation adhere better on skin and lengthens the longevity of the foundation. Moreover, it gives a brighter skin tone so that you can have a better finish

Directions

Directions: Apply basic makeup such as moisturizer and sunscreen. Then, place primer on face by using a makeup brush or sponge. Pat on lightly for a smooth finish.